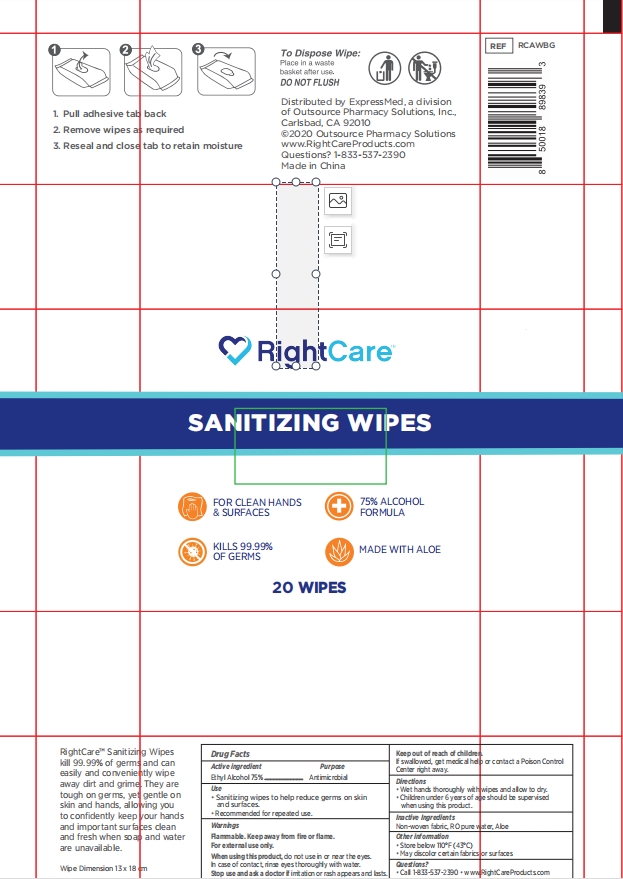 DRUG LABEL: RightCare Sanitizing  wipes
NDC: 58428-002 | Form: CLOTH
Manufacturer: OUTSOURCE PHARMACY SOLUTIONS INC.
Category: otc | Type: HUMAN OTC DRUG LABEL
Date: 20201009

ACTIVE INGREDIENTS: ALCOHOL 45 mL/20 1
INACTIVE INGREDIENTS: POLYESTER (ADIPIC ACID, 1,6-HEXANEDIOL, NEOPENTYL GLYCOL); ALOE; WATER; DIRECT BLACK 19

DOSAGE AND ADMINISTRATION

Store below 110°F (43°C)

INACTIVE INGREDIENT

water,Polyester,Viscose, ALOE

INDICATIONS AND USAGE

1. Pull adhesive tab back
2. Remove wipes as required
3. Reseal and close tab to retain moisture

ACTIVE INGREDIENT

Alcohol

KEEP OUT OF REACH OF CHILDREN

Children under 6 years of age should be supervised when using this product.

PURPOSE

Disinfection
Sterilization
No Rinseing

WARNINGS

Flammable. Keep away from fire or flame.For external use only.